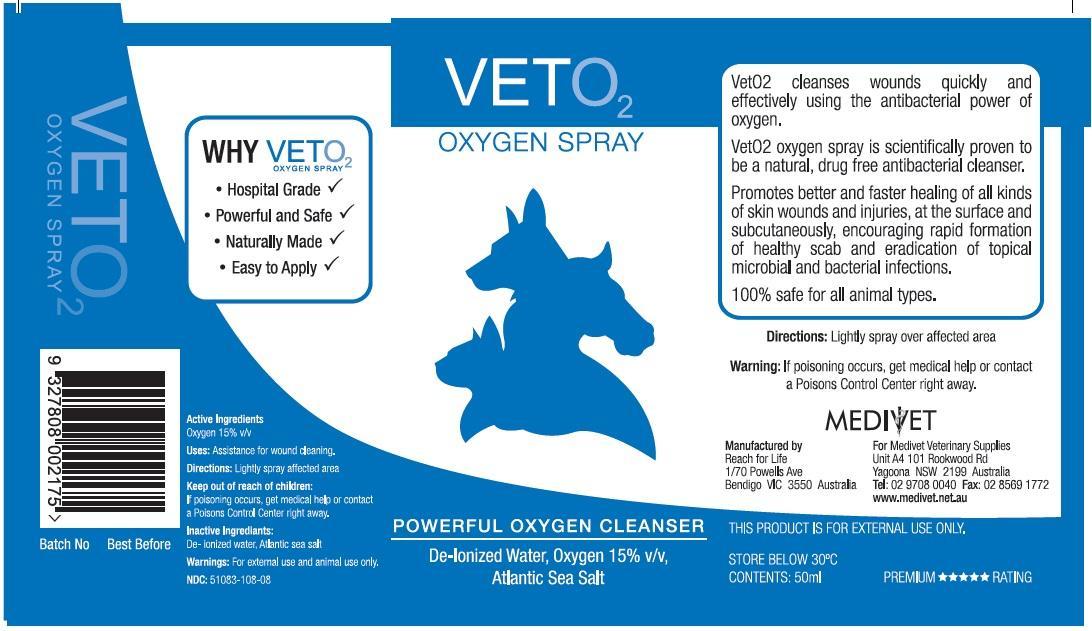 DRUG LABEL: Vet O2
NDC: 51083-108 | Form: SPRAY
Manufacturer: Medivet Pty Ltd
Category: animal | Type: OTC ANIMAL DRUG LABEL
Date: 20130306

ACTIVE INGREDIENTS: OXYGEN 15 mL/100 mL

Active Ingredient

ACTIVE INGREDIENT

Oxygen 15 % V/V - 15 ml/100 ml

Purpose

Wound Cleanser

Indication and Usage Section.

Used in the cleansing of wound.

Warnings

For external use only. In case of accidental ingestion, get medical help or contact a Poisons Control Center right away

Directions for Use

After thoroughly cleaning the wound or sorearea it is sprayed directly onto the skin and coveredwith a light bandage to keep the area clean.

Inactive Ingredients

Atlantic Sea Salt and De-ionised water.

Keep Out of reach of Children

PACKAGE LABEL

For Animal Use Only.

Manufactured By :

Reach for Life

1/70 Powells Ave

Bendigo VIC 3550

Australia

Manufactured For:

Medivet Veterinary Supplies

U4A 101 Rookwood Rd,
YAGOONA, NSW 2199, Australia

Store Below 30 o C.